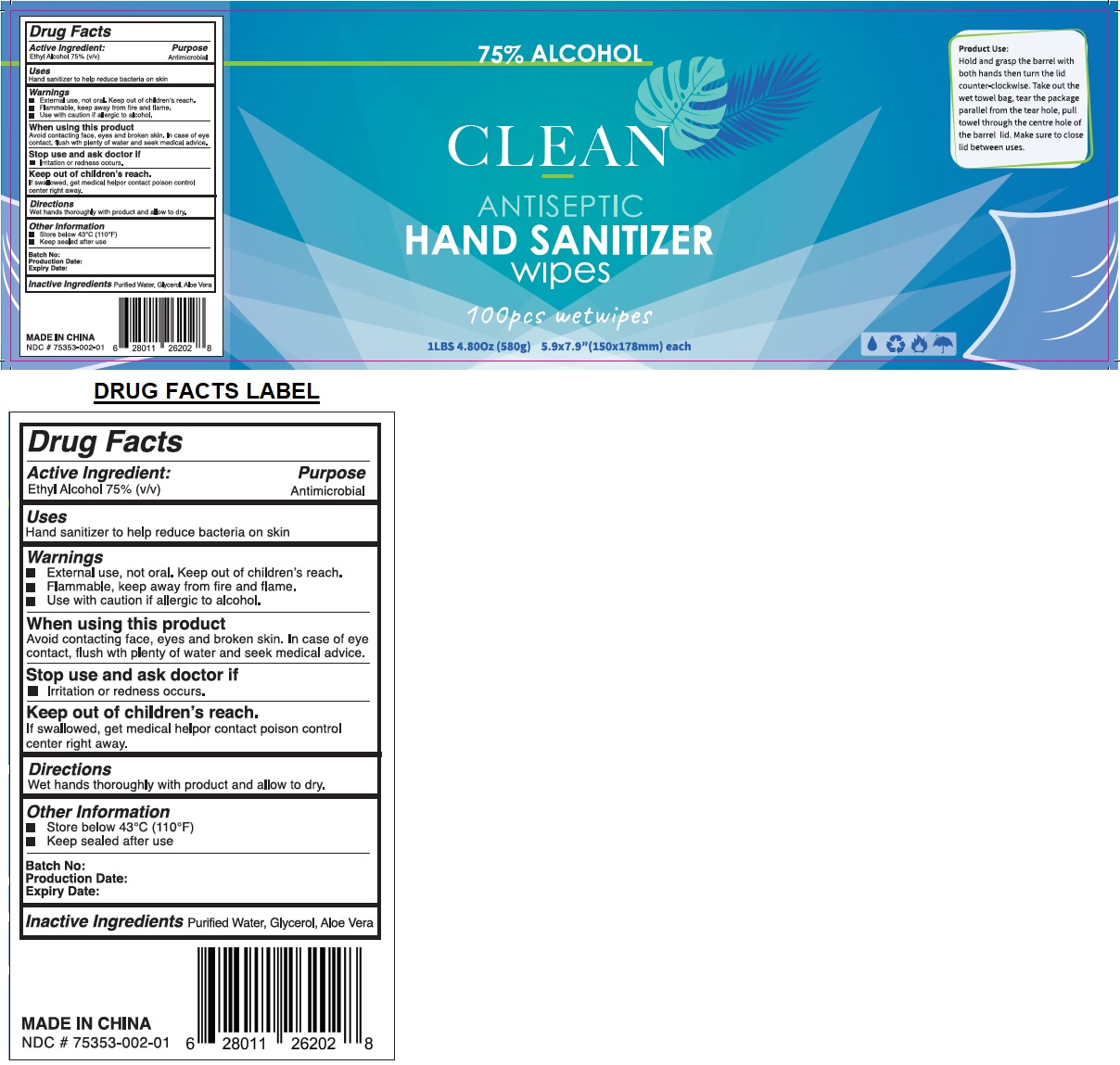 DRUG LABEL: CLEAN ANTISEPTIC HAND SANITIZER wipes
NDC: 75353-002 | Form: CLOTH
Manufacturer: Raw Office Inc, The
Category: otc | Type: HUMAN OTC DRUG LABEL
Date: 20230718

ACTIVE INGREDIENTS: ALCOHOL 75 mL/100 mL
INACTIVE INGREDIENTS: WATER; GLYCERIN; ALOE VERA LEAF

CLEAN ANTISEPTIC HAND SANITIZER wipes

Active Ingredient:

Ethyl Alcohol 75% (v/v)

Purpose

Antimicrobial

Uses

Hand sanitizer to help reduce bacteria on skin

Warnings

■ External use, not oral. Keep out of children's reach.

■ Flammable, keep away from fire and flame.

■ Use with caution if allergic to alcohol.

When using this product

Avoid contacting face, eyes and broken skin. In case of eye contact, flush with plenty of water and seek medical advice.

Stop use and ask doctor if

■ Irritation or redness occurs.

Keep out of children's reach.

If swallowed, get medical help or contact poison control center right away.

Directions

Wet hands thoroughly with product and allow to dry.

Other Information

■ Store below 43°C (110°F)

■ Keep sealed after use

Inactive IngredientsPurified Water, Glycerol, Aloe Vera

Product Use:

Hold and grasp the barrel with both hands then turn the lid counter-clockwise. Take out the wet towel bag, tear the package parallel from the tear hole, pull towel through the centre hole of the barrel lid. Make sure to close lid between uses.

MADE IN CHINA